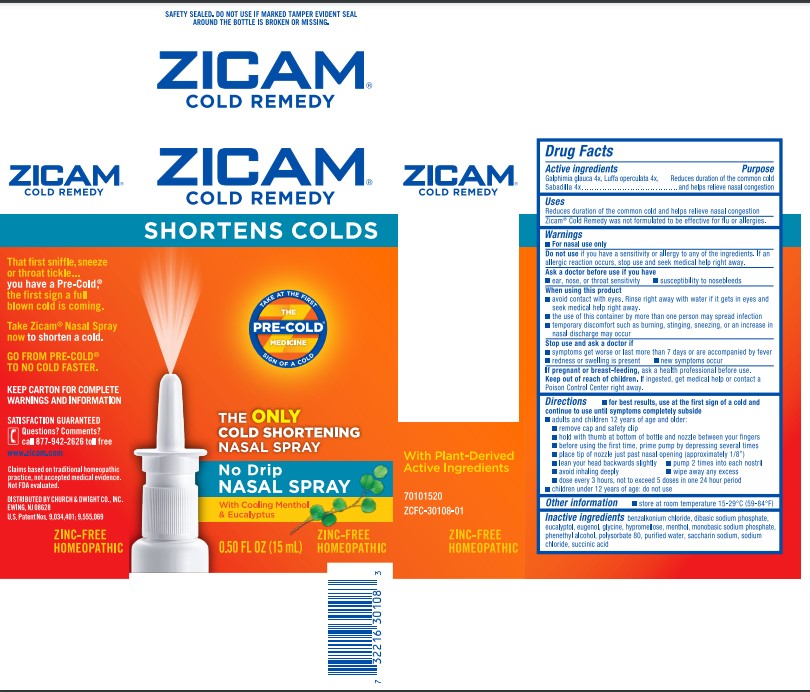 DRUG LABEL: Zicam Cold Remedy
NDC: 10237-474 | Form: SPRAY
Manufacturer: Church & Dwight Co., Inc.
Category: homeopathic | Type: HUMAN OTC DRUG LABEL
Date: 20241119

ACTIVE INGREDIENTS: GALPHIMIA GLAUCA FLOWERING TOP 4 [hp_X]/0.56 mL; LUFFA OPERCULATA FRUIT 4 [hp_X]/0.56 mL; SCHOENOCAULON OFFICINALE SEED 4 [hp_X]/0.56 mL
INACTIVE INGREDIENTS: BENZALKONIUM CHLORIDE; SODIUM PHOSPHATE, DIBASIC, UNSPECIFIED FORM; EUCALYPTOL; EUGENOL; GLYCINE; HYPROMELLOSE, UNSPECIFIED; MENTHOL, UNSPECIFIED FORM; SODIUM PHOSPHATE, MONOBASIC, UNSPECIFIED FORM; PHENYLETHYL ALCOHOL; POLYSORBATE 80; WATER; SACCHARIN SODIUM; SODIUM CHLORIDE; SUCCINIC ACID

ZICAM® COLD REMEDY No Drip NASAL SPRAY

Drug Facts

Active ingredients

Galphimia glauca 4x, Luffa operculata 4x, Sabadilla 4x

Purpose

Reduces duration of the common cold and helps relieve nasal congestion

Uses

Reduces duration of the common cold and helps relieve nasal congestion

---------------------------------------------------------------------------------------------------

Zicam® Cold Remedy was not formulated to be effective for flu or allergies.

Warnings

- For nasal use only

Do not use if you have a sensitivity or allergy to any of the ingredients. If an allergic reaction occurs, stop use and seek medical help right away.

Ask a doctor before use if you have

- ear, nose, or throat sensitivity
- susceptibility to nosebleeds

When using this product

- avoid contact with eyes. Rinse right away with water if it gets in eyes and seek medical help right away.
- the use of this container by more than one person may spread infection
- temporary discomfort such as burning, stinging, sneezing, or an increase in nasal discharge may occur

Stop use and ask a doctor if

- symptoms get worse or last more than 7 days or are accompanied by fever
- redness or swelling is present
- new symptoms occur

PREGNANCY OR BREAST FEEDING

If pregnant or breast-feeding, ask a health professional before use.

Keep out of reach of children. If swallowed, get medical help or contact a Poison Control Center right away.

Directions

- for best results, use at the first sign of a cold and continue to use until symptoms completely subside
- adults and children 12 years of age and older:
  - remove cap and safety clip
  - hold with thumb at bottom of bottle and nozzle between your fingers
  - before using the first time, prime pump by depressing several times
  - place tip of nozzle just past nasal opening (approximately 1/8")
  - lean your head backwards slightly
  - pump 2 times into each nostril
  - avoid inhaling deeply
  - wipe away any excess
  - dose every 3 hours, not to exceed 5 doses in one 24 hour period
- children under 12 years of age: do not use

Other information

- store at room temperature 15-29°C (59-84°F)

Inactive ingredients

benzalkonium chloride, dibasic sodium phosphate, eucalyptol, eugenol, glycine, hypromellose, menthol, monobasic sodium phosphate, phenethyl alcohol, polysorbate 80, purified water, saccharin sodium, sodium chloride, succinic acid

Questions? Comments?

call 877-942-2626 toll free

www.zicam.com

PRINCIPAL DISPLAY PANEL - 15 mL Bottle Carton

ZICAM®

COLD REMEDY

SHORTENS COLDS

TAKE AT THE FIRST

THE
PRE-COLD®
MEDICINE

SIGN OF A COLD

THE
ONLY
COLD SHORTENING
NASAL SPRAY

No Drip
NASAL SPRAY

With Cooling Menthol
& Eucalyptus

0.50 FL OZ (15 mL)

ZINC-FREE
HOMEOPATHIC